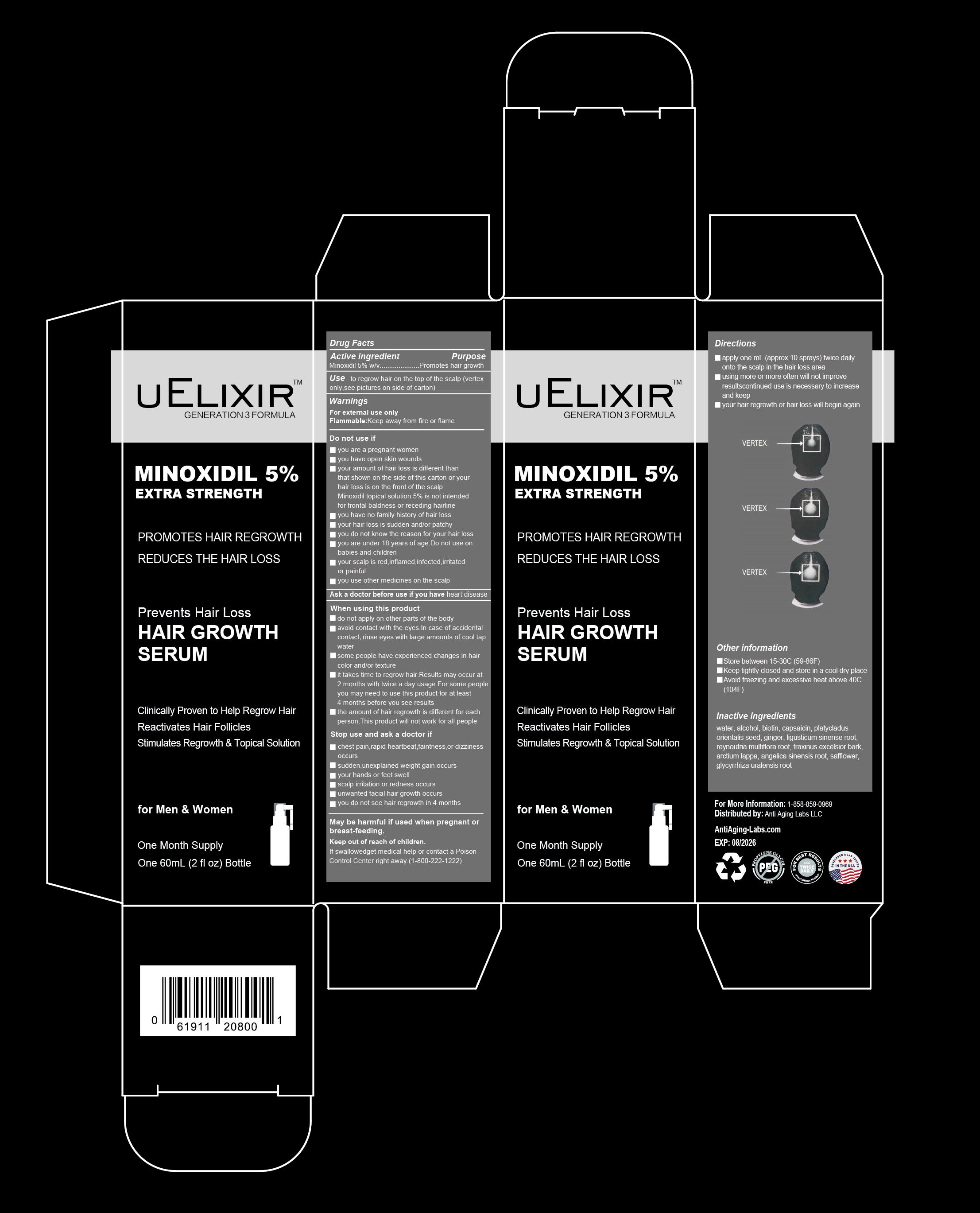 DRUG LABEL: uElixir Hair Growth Serum
NDC: 82607-002 | Form: SOLUTION
Manufacturer: ANTI AGING LABS LLC
Category: otc | Type: HUMAN OTC DRUG LABEL
Date: 20221115

ACTIVE INGREDIENTS: MINOXIDIL 5 g/100 mL
INACTIVE INGREDIENTS: PLATYCLADUS ORIENTALIS SEED; REYNOUTRIA MULTIFLORA ROOT; WATER; CAPSAICIN; GINGER; BIOTIN; ALCOHOL; LIGUSTICUM SINENSE SUBSP. CHUANXIONG ROOT; ARCTIUM LAPPA WHOLE; GLYCYRRHIZA URALENSIS ROOT; FRAXINUS EXCELSIOR BARK; ANGELICA SINENSIS ROOT; SAFFLOWER

Active ingredient

Minoxidil 5% w/v

Purpose

Promotes hair growth

Use

to regrow hair on the top of the scalp (vertex only,see pictures on side of carton)

Warnings

For external use only
Extremely Flammable: Avoid fire, flame, or smoking during and immediately following application.

Do not use if

- you are a pregnant women
- you have open skin wounds
- your amount of hair loss is different than that shown on the side of this carton or your hair loss is on the front of the scalp. Minoxidil topical solution 5% is not intended for frontal baldness or receding hairline.
- you have no family history of hair loss
- your hair loss is sudden and/or patchy
- you do not know the reason for your hair loss
- you are under 18 years of age. Do not use on babies and children.
- your scalp is red,inflamed,infected,irritated or painful
- you use other medicines on the scalp

Ask a doctor before use if you have

heart disease

When using this product

- do not apply on other parts of the body
- avoid contact with the eyes. In case of accidental contact,rinse eyes with large amounts of cool tap water.
- some people have experienced changes in hair color and/or texture
- it takes time to regrow hair.Results may occur at 2 months with twice a day usage. For some people you may need to use this product for at least 4 months before you see results.
- the amount of hair regrowth is different for each person.This product will not work for all people.

Stop use and ask a doctor if

- chest pain,rapid heartbeat,faintness,or dizziness occurs
- sudden,unexplained weight gain occurs
- your hands or feet swell
- scalp irritation or redness occurs
- unwanted facial hair growth occurs
- you do not see hair regrowth in 4 months

Keep out of reach of children.

If swallowed, get medical help or contact a Poison Control Center right away. (1-800-222-1222)

Directions

- apply one mL with dropper 2 times a day directly onto the scalp in the hair loss area
- using more or more often will not improve results
- continued use is necessary to increase and keep your hair regrowth, or hair loss will begin again

Other information

- Store between 15-30C (59-86F)
- Avoid freezing and excessive heat above 40C (104F)

Inactive ingredients

water, vitamin H (biotin), alcohol, ginger extract, carthamus tinctorius (safflower) flower extract, fraxinus excelsior bark extract, fructus acerola extract, ligusticum chuanxiong root extract, glycyrrhiza uralensis (licorice) root extract, arctium lappa langelica sinensis root extract, thuja orientalis seed extract, polygonum multiflorum root extract, capsaicin

For More Information:

1-858-859-0969